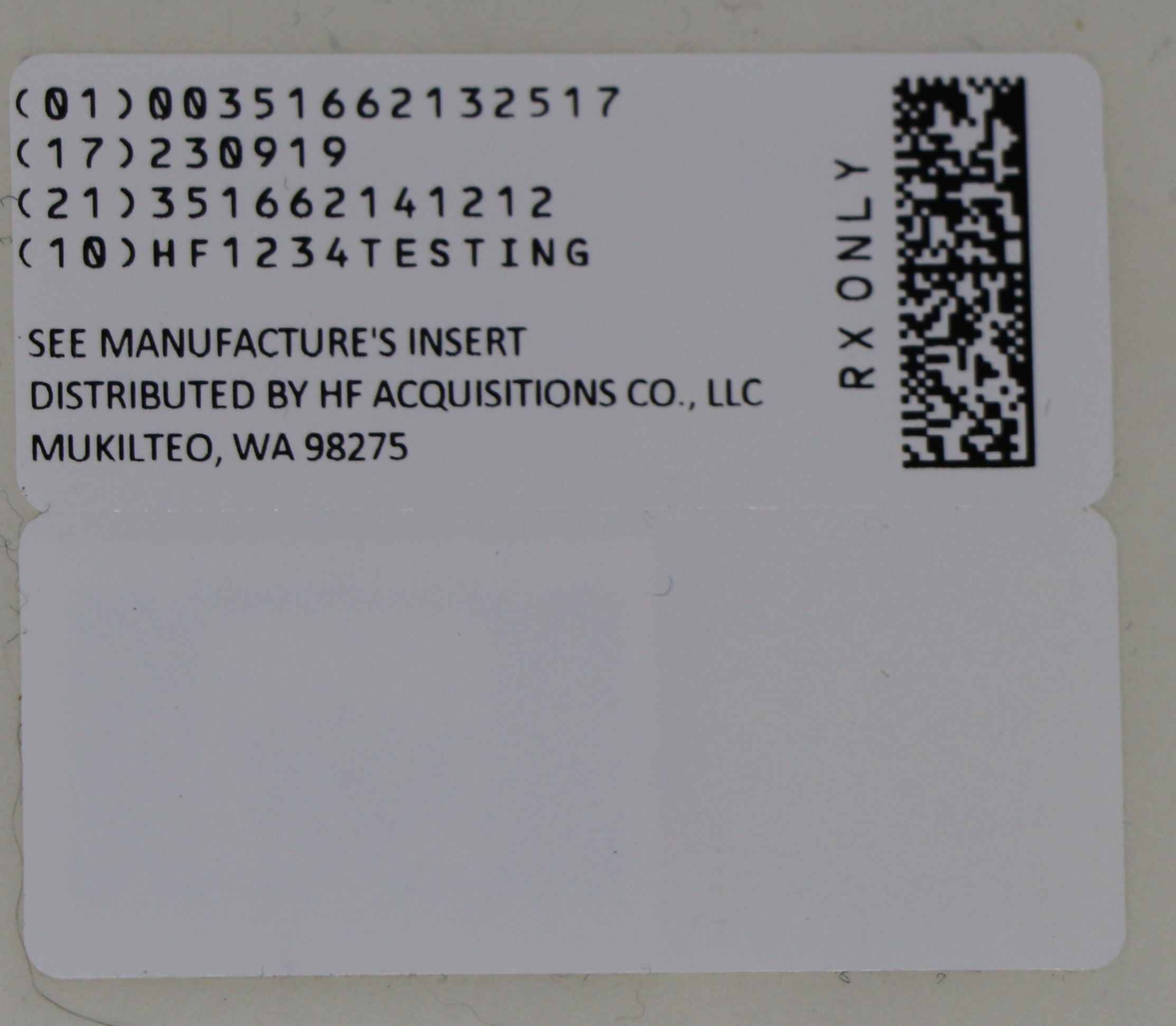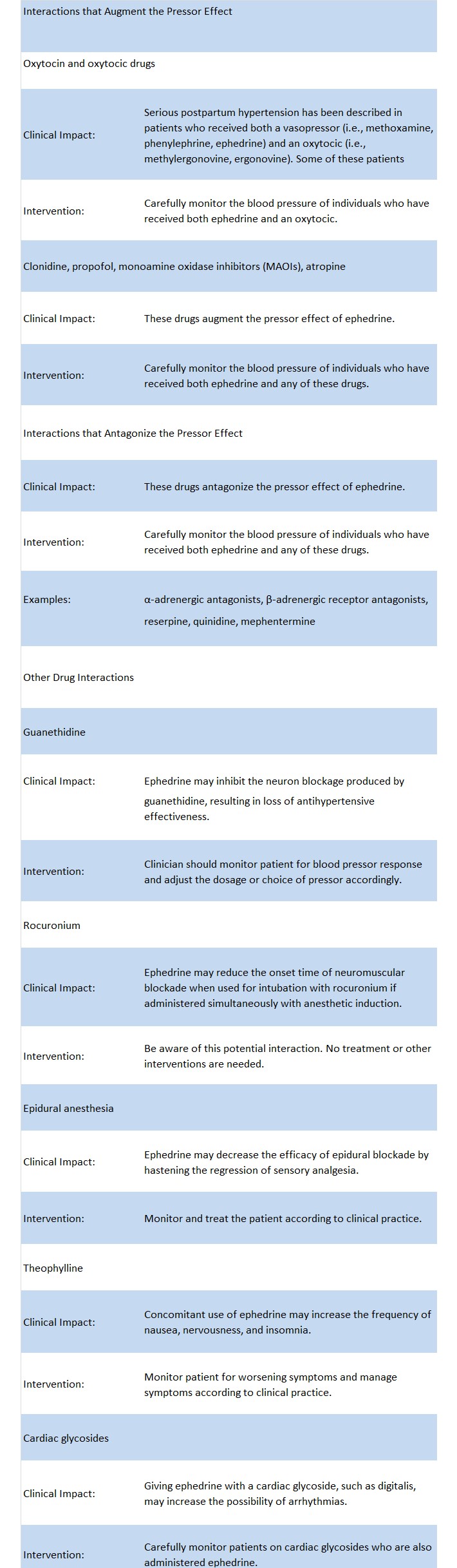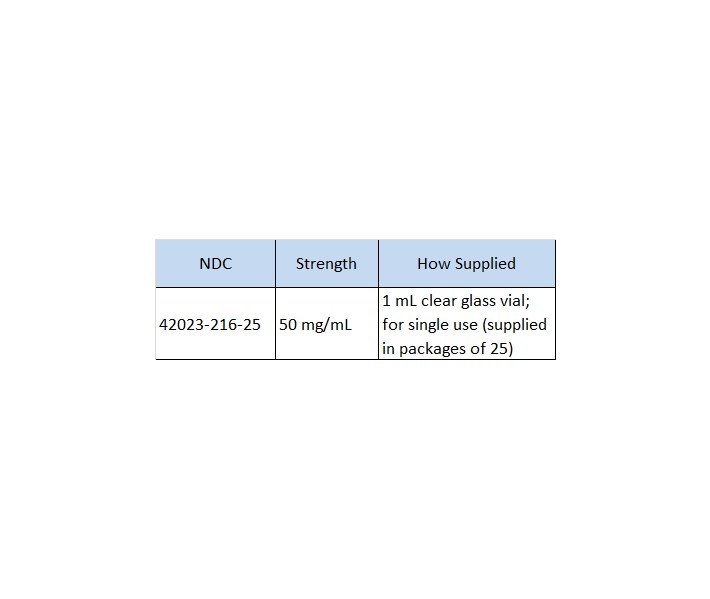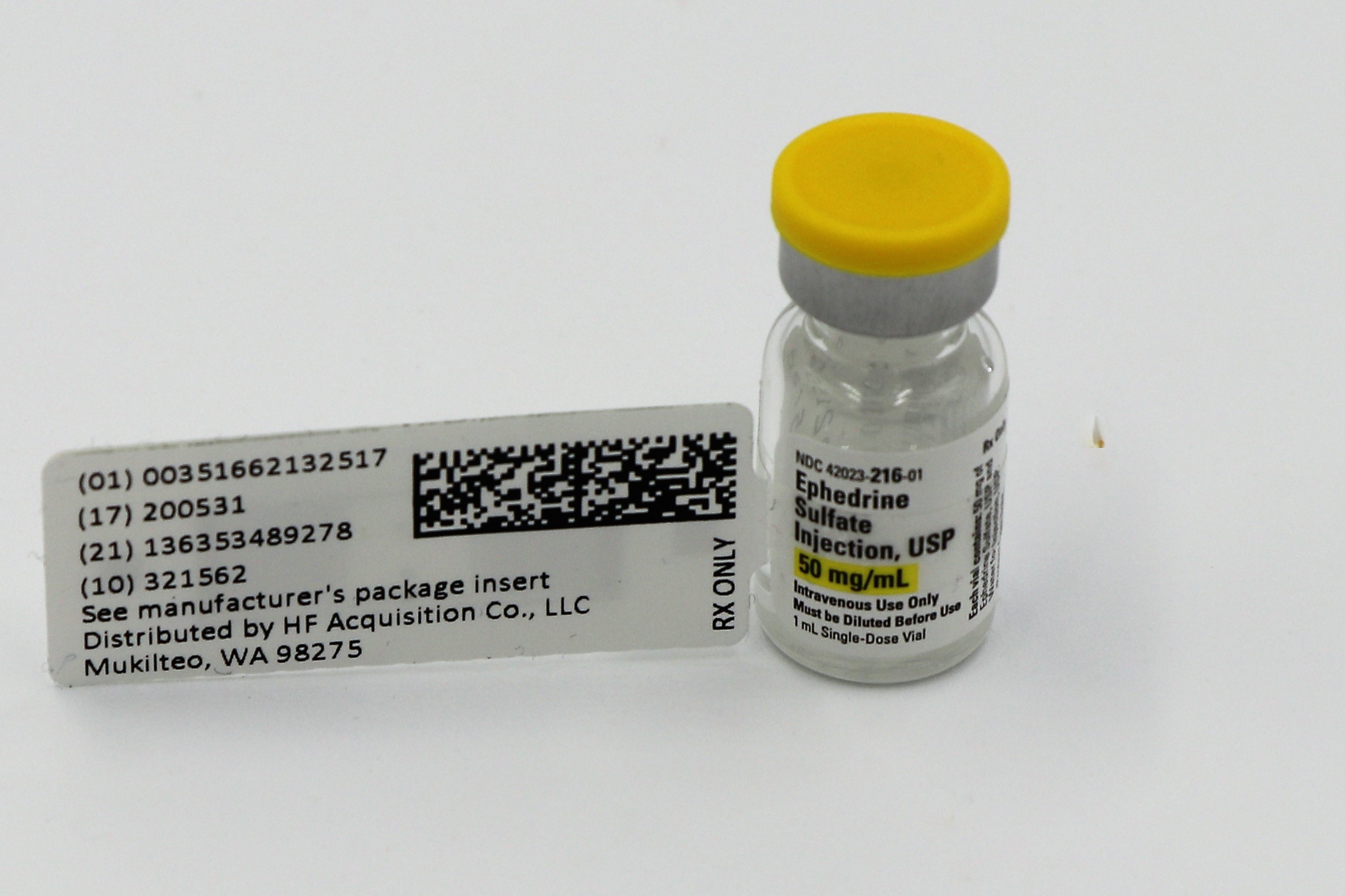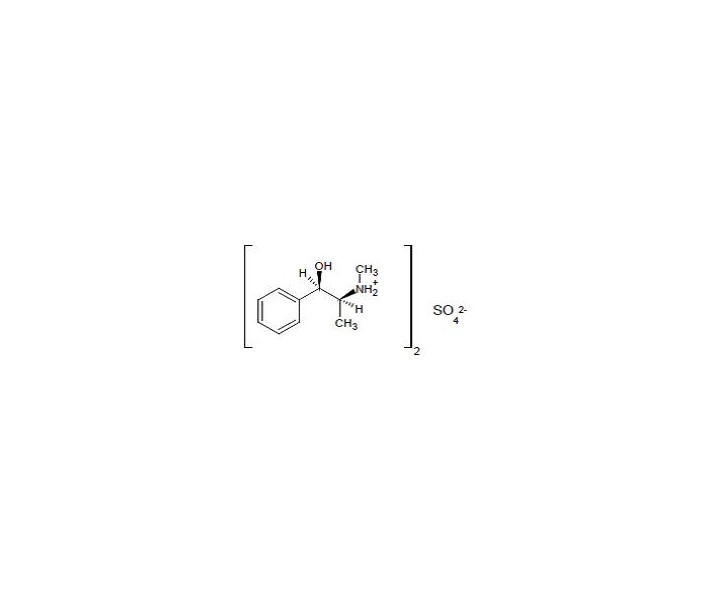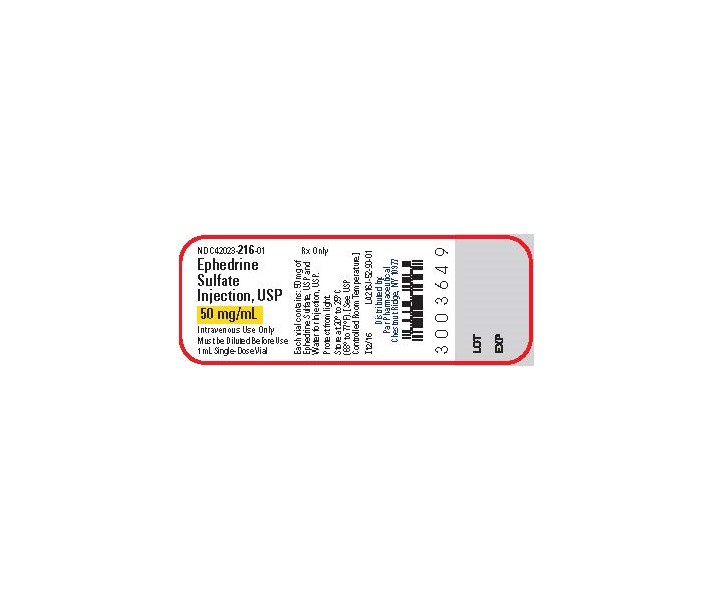 DRUG LABEL: EPHEDRINE SULFATE
NDC: 51662-1325 | Form: INJECTION, SOLUTION
Manufacturer: HF Acquisition Co LLC, DBA HealthFirst
Category: prescription | Type: HUMAN PRESCRIPTION DRUG LABEL
Date: 20240226

ACTIVE INGREDIENTS: EPHEDRINE SULFATE 50 mg/1 mL
INACTIVE INGREDIENTS: WATER

EPHEDRINE SULFATE INJECTIONS, USP 50 mg/mL 1mL VIAL

HIGHLIGHTS OF PRESCRIBING INFORMATION

These highlights do not include all the information needed to use EPHEDRINE SULFATE INJECTION safely and effectively. See full prescribing information for EPHEDRINE SULFATE INJECTION.
EPHEDRINE SULFATE injection, USP, for intravenous use
Initial U.S. Approval: 2016

INDICATIONS AND USAGE

Ephedrine Sulfate Injection, USP is an alpha- and beta- adrenergic agonist and a norepinephrine-releasing agent indicated for the treatment of clinically important hypotension occurring in the setting of anesthesia. (1)

DOSAGE AND ADMINISTRATION

Treatment of hypotension developing during anesthesia: Bolus intravenous injection: 5 to 10 mg as needed, not to exceed 50 mg. Dilute before use. See Full Prescribing Information for instructions on administration and preparation for injection. (2)

DOSAGE FORMS AND STRENGTHS

Injection: 50 mg/mL ephedrine sulfate in single-dose vial (3)

CONTRAINDICATIONS

None (4)

WARNINGS AND PRECAUTIONS

• Pressor Effect with Concomitant Oxytocic Drugs: Pressor effect of sympathomimetic pressor amines is potentiated (5-5.1)

• Tachyphylaxis and Tolerance: Repeated administration of ephedrine may cause tachyphylaxis (5-5.2)

ADVERSE REACTIONS

Most common adverse reactions during treatment: nausea, vomiting, and tachycardia.(6)

To report SUSPECTED ADVERSE REACTIONS, contact Par Pharmaceutical at 1-800-828-9393 or FDA at 1-800-FDA-1088 or www.fda.gov/medwatch.

DRUG INTERACTIONS

• Interactions that Augment the Pressor Effect: clonidine, oxytocin and oxytocic drugs, propofol, monoamine oxidase inhibitors (MAOIs), and atropine. Monitor blood pressure. (7)

• Interactions that Antagonize the Pressor Effect: Antagonistic effects with α-adrenergic antagonists, β-adrenergic antagonists, reserpine, quinidine, mephentermine. Monitor blood pressure. (7)

• Guanethidine: Ephedrine may inhibit the neuron blockage produced by guanethidine, resulting in loss of antihypertensive effectiveness. Monitor blood pressure and adjust the dosage of pressor accordingly. (7)

• Rocuronium: Ephedrine may reduce the onset time of neuromuscular blockade when used for intubation with rocuronium if administered simultaneously with anesthetic induction. Be aware of this potential interaction. No treatment or other interventions are needed. (7)

• Epidural anesthesia: Ephedrine may decrease the efficacy of epidural blockade by hastening the regression of sensory analgesia. Monitor and treat the patient according to clinical practice. (7)

• Theophylline: Concomitant use of ephedrine may increase the frequency of nausea, nervousness, and insomnia. Monitor patient for worsening symptoms and manage symptoms according to clinical practice. (7)

• Cardiac glycosides: Giving ephedrine with a cardiac glycoside, such as digitalis, may increase the possibility of arrhythmias. Carefully monitor patients on cardiac glycosides who are also administered ephedrine. (7)

Revised: 1/2017

1 INDICATIONS & USAGE

Ephedrine sulfate injection is indicated for the treatment of clinically important hypotension occurring in the setting of anesthesia.

2 DOSAGE & ADMINISTRATION

2.1 General Dosage and Administration Instructions

Ephedrine sulfate injection must be diluted before administration to achieve the desired concentration as an intravenous bolus or intravenous infusion. Parenteral drug products should be inspected visually for particulate matter and discoloration prior to administration, whenever solution and container permit. Do not use if the solution is colored or cloudy, or if it contains particulate matter.

2.2 Dosing for the Treatment of Clinically Important Hypotension in the Setting of Anesthesia

The recommended dosage for the treatment of clinically important hypotension in the setting of anesthesia is an initial dose of 5 to 10 mg administered by intravenous bolus. Administer additional boluses as needed, not to exceed a total dosage of 50 mg.

Adjust dosage according to the blood pressure goal (i.e., titrate to effect).

2.3 Preparation of a 5 mg/mL Solution for Bolus Intravenous Administration

For bolus intravenous administration, prepare a solution containing a final concentration of 5 mg/mL of ephedrine sulfate injection.

Withdraw 50 mg (1 mL of 50 mg/mL) of ephedrine sulfate injection and dilute with 9 mL of 5% Dextrose Injection or Sodium Chloride Injection.

Withdraw an appropriate dose of the 5 mg/mL solution prior to bolus intravenous administration.

3 DOSAGE FORMS & STRENGTHS

Ephedrine sulfate injection is available as a single-dose 1 mL vial that contains 50 mg/mL ephedrine sulfate, equivalent to 38 mg ephedrine base.

4 CONTRAINDICATIONS

None

5 WARNINGS AND PRECAUTIONS

5.1 Pressor Effect with Concomitant Oxytocic Drugs

Serious postpartum hypertension has been described in patients who received both a vasopressor (i.e., methoxamine, phenylephrine, ephedrine) and an oxytocic (i.e., methylergonovine, ergonovine) [see Drug Interactions (7)]. Some of these patients experienced a stroke. Carefully monitor the blood pressure of individuals who have received both ephedrine and an oxytocic.

5.2 Tolerance and Tachyphylaxis

Data indicate that repeated administration of ephedrine can result in tachyphylaxis. Clinicians treating anesthesia-induced hypotension with ephedrine sulfate injection should be aware of the possibility of tachyphylaxis and should be prepared with an alternative pressor to mitigate unacceptable responsiveness.

5.3 Risk of Hypertension When Used Prophylactically

When used to prevent hypotension, ephedrine has been associated with an increased incidence of hypertension compared with when ephedrine is used to treat hypotension.

6 ADVERSE REACTIONS

The following adverse reactions associated with the use of ephedrine sulfate were identified in the literature. Because these reactions are reported voluntarily from a population of uncertain size, it is not always possible to estimate their frequency reliably or to establish a causal relationship to drug exposure.

Gastrointestinal disorders: Nausea, vomiting

Cardiac disorders: Tachycardia, palpitations (thumping heart), reactive hypertension, bradycardia, ventricular ectopics, R-R variability

Nervous system disorders: Dizziness

Psychiatric disorders: Restlessness

For medical advice about adverse reactions, contact your medical professional. To report SUSPECTED ADVERSE REACTIONS, contact Par Pharmaceutical at 1-800-828-9393 or FDA at 1-800-FDA-1088 or www.fda.gov/medwatch.

8 USE IN SPECIFIC POPULATIONS

8.1 Pregnancy

Risk Summary

Limited published data on the use of ephedrine sulfate are insufficient to determine a drug associated risk of major birth defects or miscarriage. However, there are clinical considerations [see Clinical Considerations]. Animal reproduction studies have not been conducted with ephedrine sulfate.

The estimated background risk of major birth defects and miscarriage for the indicated population is unknown. All pregnancies have a background risk of birth defect, loss, or

other adverse outcomes. In the U.S. general population, the estimated background risk of major birth defects and miscarriage in clinically recognized pregnancies is 2 to 4% and 15 to 20%, respectively.

Clinical Considerations

Fetal/Neonatal adverse reactions

Cases of potential metabolic acidosis in newborns at delivery with maternal ephedrine exposure have been reported in the literature. These reports describe umbilical artery pH of ≤7.2 at the time of delivery [see Clinical Pharmacology 12-12.3]. Monitoring of the newborn for signs and symptoms of metabolic acidosis may be required. Monitoring of infant’s acid-base status is warranted to ensure that an episode of acidosis is acute and reversible.

8.2 Lactation

Risk Summary

Limited published literature reports that ephedrine is present in human milk. However, no information is available on the effects of the drug on the breastfed infant or the effects of the drug on milk production. The developmental and health benefits of breastfeeding should be considered along with the mother's clinical need for ephedrine sulfate injection and any potential adverse effects on the breastfed child from ephedrine sulfate injection or from the underlying maternal condition.

8.4 Pediatric Use

Safety and effectiveness in pediatric patients have not been established.

8.5 Geriatric Use

Clinical studies of ephedrine did not include sufficient numbers of subjects aged 65 and over to determine whether they respond differently from younger subjects. Other reported clinical experience has not identified differences in responses between the elderly and younger patients.

In general, dose selection for an elderly patient should be cautious, usually starting at the low end of the dosing range, reflecting the greater frequency of decreased hepatic, renal, or cardiac function, and of concomitant disease or other drug therapy. This drug is known to be substantially excreted by the kidney, and the risk of adverse reactions to this drug may be greater in patients with impaired renal function. Because elderly patients are more likely to have decreased renal function, care should be taken in dose selection, and it may be useful to monitor renal function.

8.6 Renal Impairment

Ephedrine and its metabolite are excreted in urine. In patients with renal impairment, excretion of ephedrine is likely to be affected with a corresponding increase in elimination half-life, which will lead to slow elimination of ephedrine and consequently prolonged pharmacological effect and potentially adverse reactions. Monitor patients with renal impairment carefully after the initial bolus dose for adverse events.

10 OVERDOSAGE

Overdose of ephedrine can cause a rapid rise in blood pressure. In the case of an overdose, careful monitoring of blood pressure is recommended. If blood pressure continues to rise to an unacceptable level, parenteral antihypertensive agents can be administered at the discretion of the clinician.

11 DESCRIPTION

Ephedrine sulfate is an alpha- and beta-adrenergic agonist and a norepinephrine-releasing agent. Ephedrine sulfate injection, USP is a clear, colorless, sterile solution for intravenous injection. Each mL contains ephedrine sulfate 50 mg in water for injection as a single-dose product. The pH range is 4.5 to 7.0. The drug product must be diluted before intravenous administration. The chemical name of ephedrine sulfate is (1R,2S)-(-)-2-methylamine-1-phenylpropan-1-ol sulfate (2:1) (salt). Its molecular weight is 428.54.

The structural formula is:

Image 1

Ephedrine sulfate darkens on exposure to light. It is freely soluble in water and ethanol, very slightly soluble in chloroform, and practically insoluble in ether.

12 CLINICAL PHARMACOLOGY

12.1 Mechanism of Action

Ephedrine sulfate is a sympathomimetic amine that directly acts as an agonist at α- and ß adrenergic receptors and indirectly causes the release of norepinephrine from sympathetic neurons. Pressor effects by direct alpha- and beta-adrenergic receptor activation are mediated by increases in arterial pressures, cardiac output, and peripheral resistance. Indirect adrenergic stimulation is caused by norepinephrine release from sympathetic nerves.

12.2 Pharmacodynamics

Ephedrine stimulates heart rate and cardiac output and variably increases peripheral resistance; as a result, ephedrine usually increases blood pressure. Stimulation of the α-adrenergic receptors of smooth muscle cells in the bladder base may increase the resistance to the outflow of urine. Activation of ß-adrenergic receptors in the lungs promotes bronchodilation.

The overall cardiovascular effect from ephedrine is the result of a balance among α-1 adrenoceptor-mediated vasoconstriction, ß-2 adrenoceptor-mediated vasoconstriction, and ß-2 adrenoceptor-mediated vasodilatation. Stimulation of the ß-1 adrenoceptors results in positive inotrope and chronotrope action.

Tachyphylaxis to the pressor effects of ephedrine may occur with repeated administration [see Warnings and Precautions 5-5.3].

12.3 Pharmacokinetics

Publications studying pharmacokinetics of oral administration of (-)-ephedrine support that (-)-ephedrine is metabolized into norephedrine. However, the metabolism pathway is unknown. Both the parent drug and the metabolite are excreted in urine. Limited data after IV administration of ephedrine support similar observations of urinary excretion of drug and metabolite. The plasma elimination half-life of ephedrine following oral administration was about 6 hours.

Ephedrine crosses the placental barrier [see Use in Specific Populations 8-8.1].

13 NONCLINICAL TOXICOLOGY

13.1 Carcinogenesis and Mutagenesis and Impairment of Fertility

Carcinogenesis: Two-year feeding studies in rats and mice conducted under the National Toxicology Program (NTP) demonstrated no evidence of carcinogenic potential with ephedrine sulfate at doses up to 10 mg/kg/day and 27 mg/kg/day (approximately 2 times and 3 times the maximum human recommended dose on a mg/m2 basis, respectively).

Mutagenesis: Ephedrine sulfate tested negative in the in vitro bacterial reverse mutation assay, the in vitro mouse lymphoma assay, the in vitro sister chromatid exchange, and the in vitro chromosomal aberration assay.

Impairment of Fertility: Studies to evaluate the effect of ephedrine on fertility have not been conducted.

14 CLINICAL STUDIES

The evidence for the efficacy of ephedrine injection is derived from the published literature. Increases in blood pressure following administration of ephedrine were observed in 14 studies, including 9 where ephedrine was used in pregnant women undergoing neuraxial anesthesia during Cesarean delivery, 1 study in non-obstetric surgery under neuraxial anesthesia, and 4 studies in patients undergoing surgery under general anesthesia. Ephedrine has been shown to raise systolic and mean blood pressure when administered as a bolus dose following the development of hypotension during anesthesia.

16 HOW SUPPLIED

EPHEDRINE SULFATE INJECTIONS, USP is supplied in the following dosage forms.
NDC 51662-1325-1
EPHEDRINE SULFATE INJECTIONS, USP 50 mg/mL 1mL VIAL

HF Acquisition Co LLC, DBA HealthFirst
Mukilteo, WA 98275

Also supplied in the following manufacture supplied dosage forms

Ephedrine Sulfate Injection, USP, 50 mg/mL, is supplied as follows:

Vial stoppers are not manufactured with natural rubber latex.

Store ephedrine sulfate injection, 50 mg/mL, at 20° to 25°C (68° to 77°F), with excursions permitted to 15°C to 30°C (59°F to 86°F) [See USP Controlled Room Temperature.] Protect from light. Store in carton until time of use. For single use only. Discard unused portion.

SPL UNCLASSIFIED

Distributed by:

Par Pharmaceutical

Chestnut Ridge, NY 10977

R1/17

PRINCIPAL DISPLAY PANEL, VIAL LABEL

Ephedrine Sulfate Injection, USP

50 mg/mL, 1 mL Single-Dose Vial